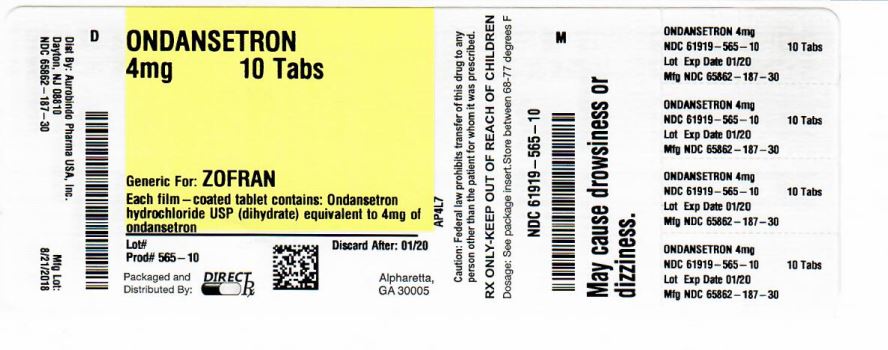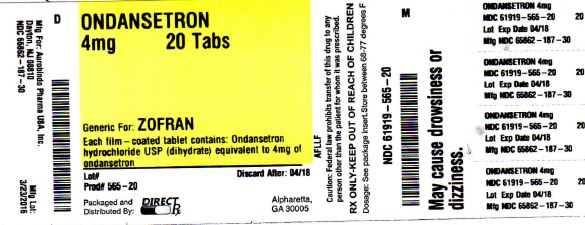 DRUG LABEL: ONDANSETRON
NDC: 61919-565 | Form: TABLET, FILM COATED
Manufacturer: DIRECT RX
Category: prescription | Type: HUMAN PRESCRIPTION DRUG LABEL
Date: 20180912

ACTIVE INGREDIENTS: ONDANSETRON HYDROCHLORIDE 4 mg/1 1
INACTIVE INGREDIENTS: ANHYDROUS LACTOSE; CELLULOSE, MICROCRYSTALLINE; MAGNESIUM STEARATE; STARCH, CORN; TITANIUM DIOXIDE; HYPROMELLOSE 2910 (6 MPA.S); TRIACETIN

ONDANSETRON 4mg

INDICATIONS AND USAGE

1. Prevention of nausea and vomiting associated with highly emetogenic cancer chemotherapy.
2. Prevention of nausea and vomiting associated with initial and repeat courses of moderately emetogenic cancer chemotherapy.
3. Prevention of nausea and vomiting associated with radiotherapy in patients receiving either total body irradiation, single high-dose fraction to the abdomen, or daily fractions to the abdomen.
4. Prevention of postoperative nausea and/or vomiting. As with other antiemetics, routine prophylaxis is not recommended for patients in whom there is little expectation that nausea and/or vomiting will occur postoperatively. In patients where nausea and/or vomiting must be avoided postoperatively, ondansetron tablets, USP are recommended even where the incidence of postoperative nausea and/or vomiting is low.